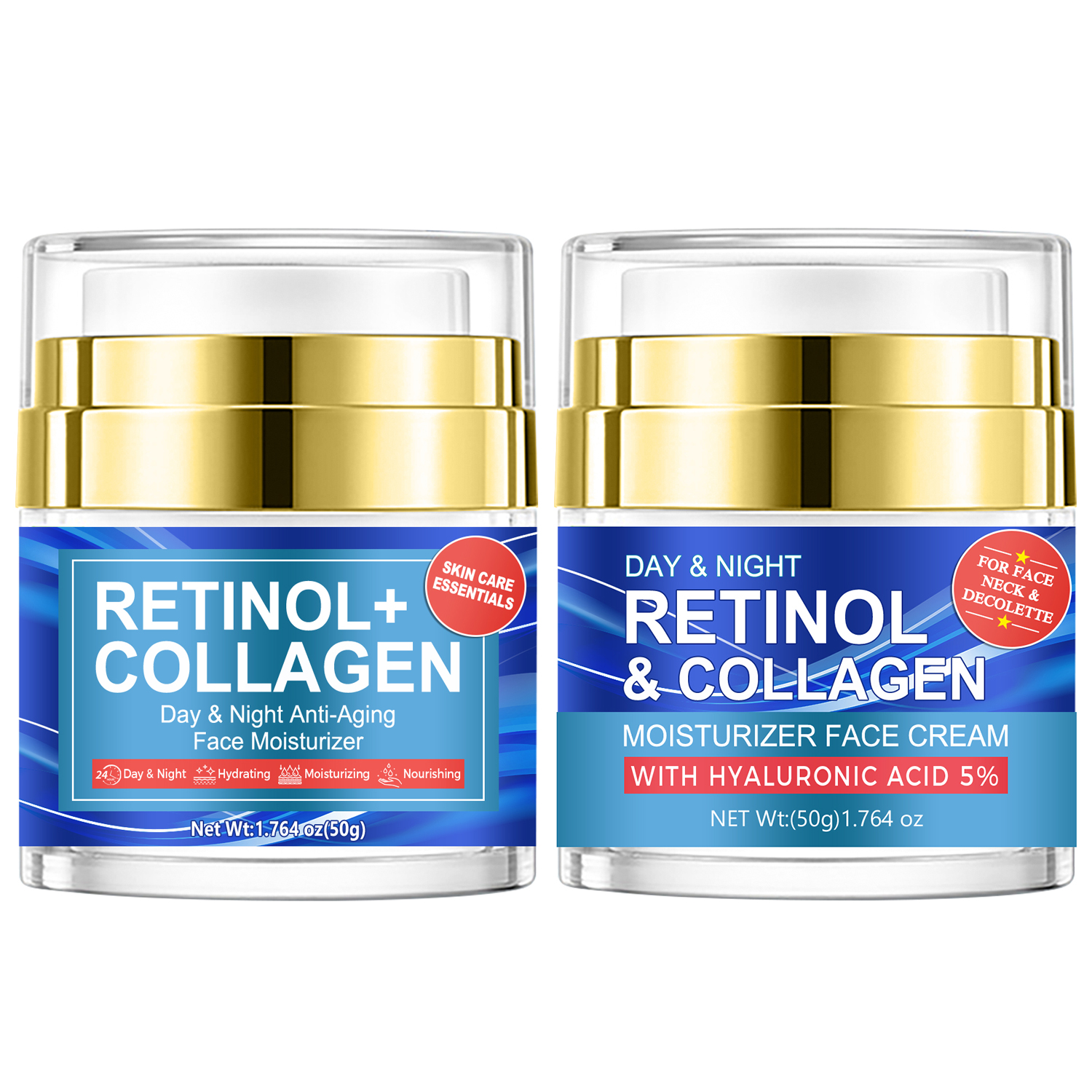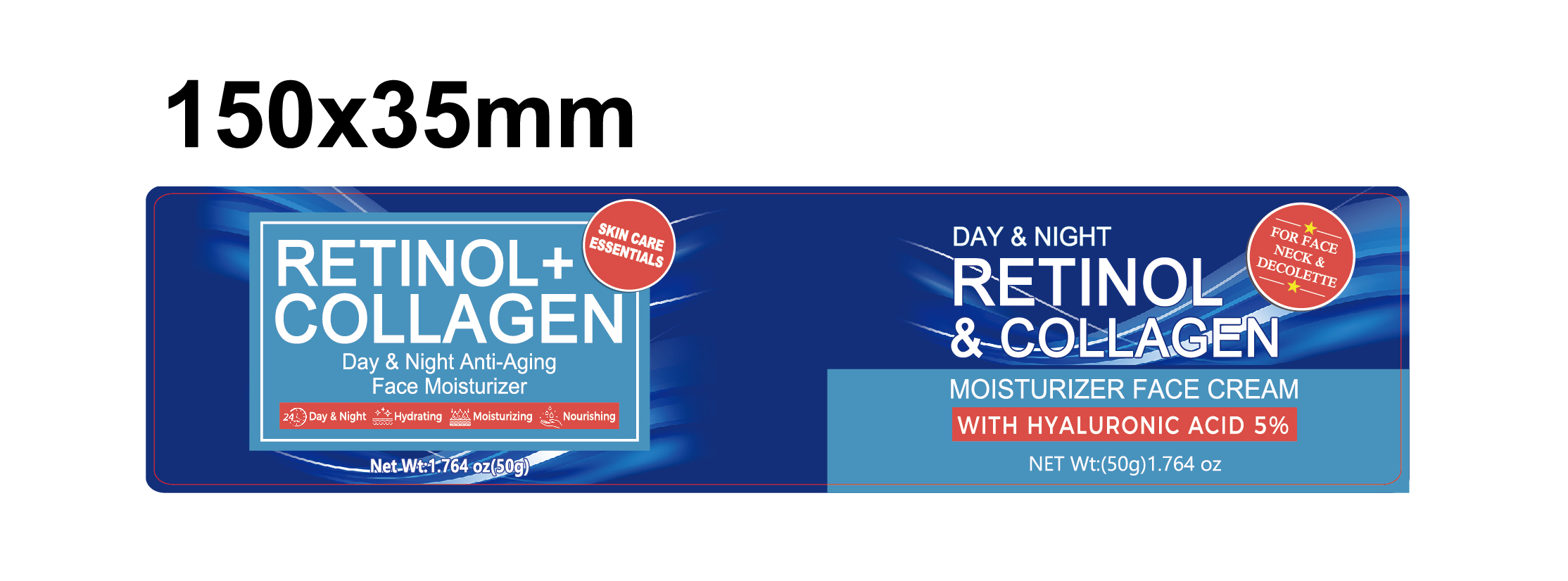 DRUG LABEL: Face Moisturizer
NDC: 84025-182 | Form: CREAM
Manufacturer: Guangzhou Yanxi Biotechnology Co.. Ltd
Category: otc | Type: HUMAN OTC DRUG LABEL
Date: 20240906

ACTIVE INGREDIENTS: GLYCERIN 5 mg/50 g; BUTYLENE GLYCOL 3 mg/50 g
INACTIVE INGREDIENTS: WATER

DOSAGE AND ADMINISTRATION

Moisturizing cream for skin care

WARNINGS

Keep out of children

INACTIVE INGREDIENT

AQUA

INDICATIONS AND USAGE

for daily skin care

keep out of children

PURPOSE

Effectively moisturizes the skin and keeps it firm